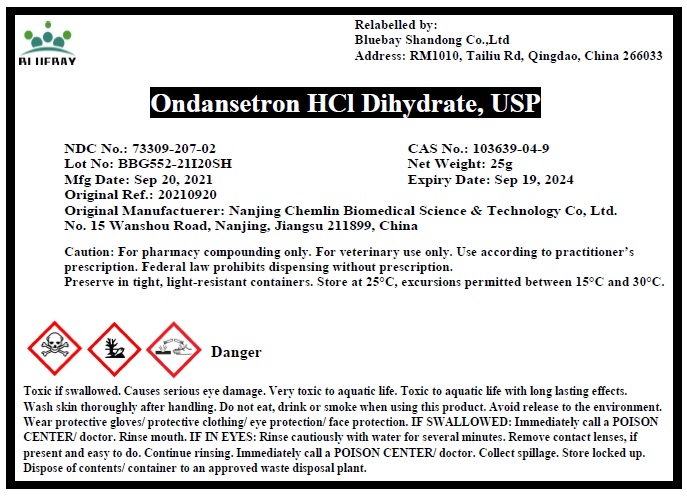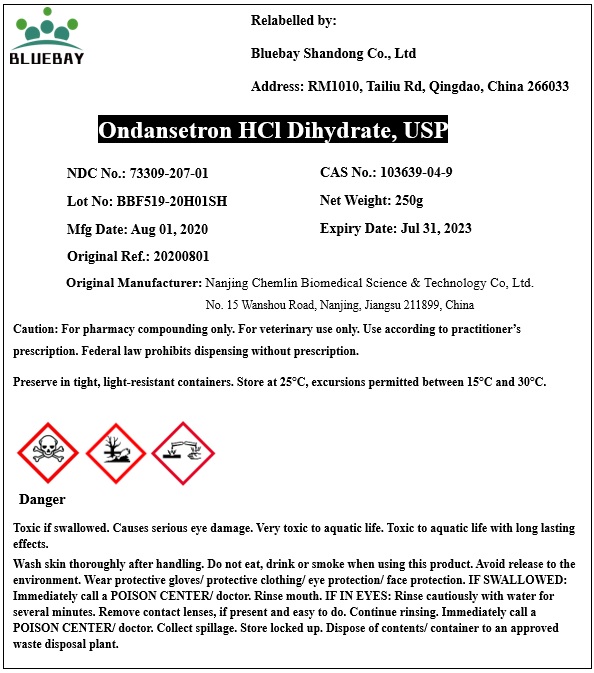 DRUG LABEL: Ondansetron HCl dihydrate
NDC: 73309-207 | Form: POWDER
Manufacturer: BLUEBAY SHANDONG CO.,LTD
Category: other | Type: BULK INGREDIENT
Date: 20211021

ACTIVE INGREDIENTS: ONDANSETRON HYDROCHLORIDE 1 g/1 g

Ondansetron HCl dihydrate